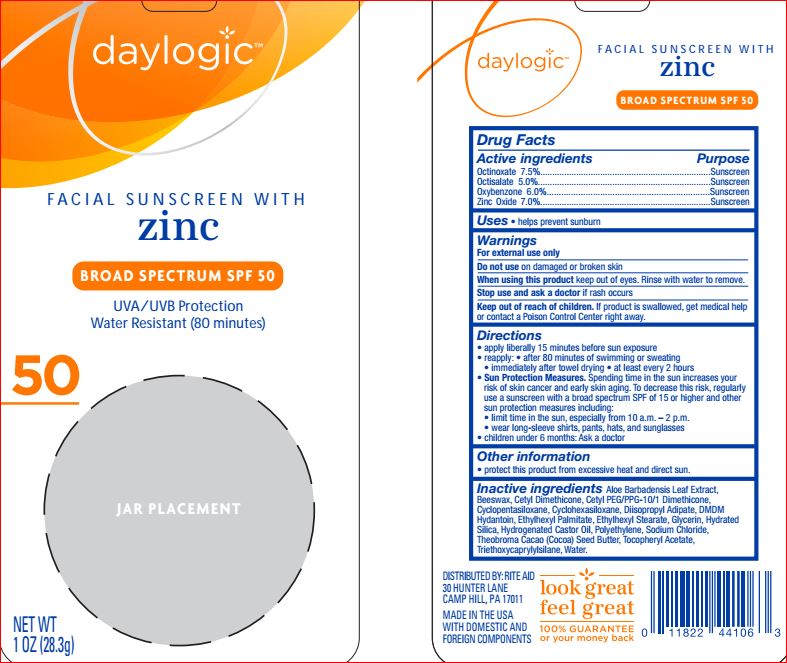 DRUG LABEL: Facial Sunscreen with Zinc SPF 50
NDC: 11822-1214 | Form: CREAM
Manufacturer: Rite Aid
Category: otc | Type: HUMAN OTC DRUG LABEL
Date: 20180511

ACTIVE INGREDIENTS: Octinoxate 7.5 g/100 g; Octisalate 5 g/100 g; Oxybenzone 6 g/100 g; Zinc Oxide 7 g/100 g
INACTIVE INGREDIENTS: ALOE VERA LEAF; YELLOW WAX; CYCLOMETHICONE 6; CYCLOMETHICONE 5; Diisopropyl Adipate; DMDM HYDANTOIN; Ethylhexyl Palmitate; Ethylhexyl Stearate; Glycerin; Hydrated Silica; Hydrogenated Castor Oil; HIGH DENSITY POLYETHYLENE; Sodium Chloride; COCOA BUTTER; .ALPHA.-TOCOPHEROL ACETATE; Triethoxycaprylylsilane; Water

Drug Facts

Active ingredients Purpose
Octinoxate 7.5%.......................................................................Sunscreen
Octisalate 5.0%........................................................................Sunscreen
Oxybenzone 6.0%...................................................................Sunscreen
Zinc Oxide 7.0%.......................................................................Sunscreen

INDICATIONS AND USAGE

Uses • helps prevent sunburn

Warnings
For external use only
Do not use on damaged or broken skin
When using this product keep out of eyes. Rinse with water to remove.
Stop use and ask a doctor if rash occurs

Keep out of reach of children. If product is swallowed, get medical help or contact a Poison Control Center right away.

Directions
• apply liberally 15 minutes before sun exposure
• reapply: • after 80 minutes of swimming or sweating
• immediately after towel drying • at least every 2 hours
• Sun Protection Measures. Spending time in the sun increases your
risk of skin cancer and early skin aging. To decrease this risk, regularly
use a sunscreen with a broad spectrum SPF of 15 or higher and other
sun protection measures including:
• limit time in the sun, especially from 10 a.m. – 2 p.m.
• wear long-sleeve shirts, pants, hats, and sunglasses
• children under 6 months: Ask a doctor

Other information
• protect this product from excessive heat and direct sun.

Inactive ingredients

Aloe Barbadensis Leaf Extract,
Beeswax, Cetyl Dimethicone, Cetyl PEG/PPG-10/1 Dimethicone,
Cyclopentasiloxane, Cyclohexasiloxane, Diisopropyl Adipate, DMDM
Hydantoin, Ethylhexyl Palmitate, Ethylhexyl Stearate, Glycerin, Hydrated
Silica, Hydrogenated Castor Oil, Polyethylene, Sodium Chloride,
Theobroma Cacao (Cocoa) Seed Butter, Tocopheryl Acetate,
Triethoxycaprylylsilane, Water